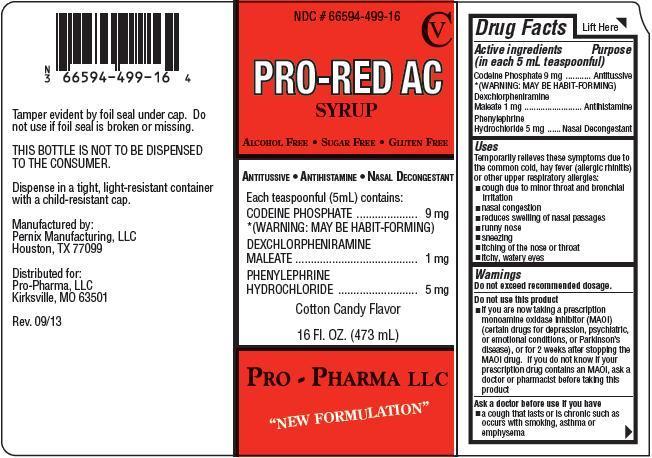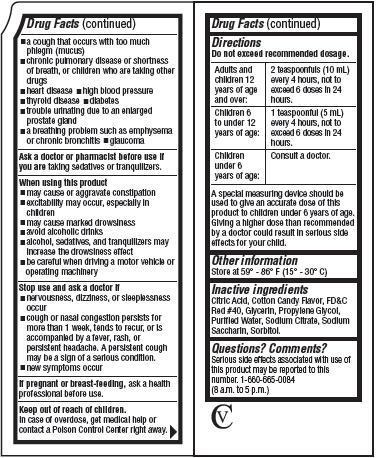 DRUG LABEL: PRO-RED
NDC: 66594-499 | Form: SYRUP
Manufacturer: Pro-Pharma, LLC
Category: otc | Type: HUMAN OTC DRUG LABEL
Date: 20131007
DEA Schedule: CV

ACTIVE INGREDIENTS: Codeine Phosphate 9 mg/5 mL; DEXCHLORPHENIRAMINE MALEATE 1 mg/5 mL; PHENYLEPHRINE HYDROCHLORIDE 5 mg/5 mL
INACTIVE INGREDIENTS: CITRIC ACID MONOHYDRATE; Glycerin; Propylene Glycol; Water; Sodium Citrate; Saccharin Sodium; Sorbitol

PRO-RED AC SYRUP

Drug Facts

Active ingredients

(in each 5 mL teaspoonful)

Codeine Phosphate 9 mg

*(WARNING: MAY BE HABIT-FORMING)

Dexchlorpheniramine Maleate 1 mg

Phenylephrine Hydrochloride 5 mg

Purpose

Antitussive

Antihistamine

Nasal Decongestant

Uses

Temporarily relieves these symptoms due to the common cold, hay fever (allergic rhinitis) or other upper respiratory allergies:

- cough due to minor throat and bronchial irritation
- nasal congestion
- reduces swelling of nasal passages
- runny nose
- sneezing
- itching of the nose or throat
- itchy, watery eyes

Warnings

Do not exceed recommended dosage.

Do not use this product

- if you are now taking a prescription monoamine oxidase inhibitor (MAOI) (certain drugs for depression, psychiatric, or emotional conditions, or Parkinson's disease), or for 2 weeks after stopping the MAOI drug. If you do not know if your prescription drug contains an MAOI, ask a doctor or pharmacist before taking this product

Ask a doctor before use if you have

- a cough that lasts or is chronic such as occurs with smoking, asthma or emphysema
- a cough that occurs with too much phlegm (mucus)
- chronic pulmonary disease or shortness of breath, or children who are taking other drugs
- heart disease
- high blood pressure
- thyroid disease
- diabetes
- trouble urinating due to an enlarged prostate gland
- a breathing problem such as emphysema or chronic bronchitis
- glaucoma

Ask a doctor or pharmacist before use if you are taking sedatives or tranquilizers.

When using this product

- may cause or aggravate constipation
- excitability may occur, especially in children
- may cause marked drowsiness
- avoid alcoholic drinks
- alcohol, sedatives, and tranquilizers may increase the drowsiness effect
- be careful when driving a motor vehicle or operating machinery

Stop use and ask a doctor if

- nervousness, dizziness, or sleeplessness occur
- cough or nasal congestion persists for more than 1 week, tends to recur, or is accompanied by a fever, rash or persistent headache. A persistent cough may be a sign of a serious condition.
- new symptoms occur

PREGNANCY OR BREAST FEEDING

If pregnant or breast-feeding, ask a health professional before use.

Keep out of the reach of children.

In case of overdose, get medical help or contact a Poison Control Center right away.

Directions

Do not exceed recommended dosage.

Adults and children 12 years of age and older: | 2 teaspoonfuls (10 mL) every 4 hours, not to exceed 6 doses in a 24 hours.
Children 6; to under 12; years of age: | 1 teaspoonful (5 mL) every 4 hours, not to exceed 6 doses in a 24 hours.
Children under 6 years of age: | Consult a doctor.

A special measuring device should be used to give an accurate dose of this product to children under 6 years of age. Giving a higher dose than recommended by a doctor could result in serious side effects for your child.

Other information

Store at 59° - 86°F (15° - 30°C)

Inactive ingredients

Citric Acid, Cotton Candy Flavor, FD&C Red #40, Glycerin, Propylene Glycol, Purified Water, Sodium Citrate, Sodium Saccharin, Sorbitol

Questions? Comments?

Serious side effects associated with use of this product may be reported to this number. 1-660-665-0084

(8 a.m. to 5 p.m.)

CV

Product Packaging

Principal display panel and side panel for 473 mL label:

NDC #66594-499-16

CV

PRO-RED AC

SYRUP

ALCOHOL FREE / SUGAR FREE / GLUTEN FREE

ANTITUSSIVE / ANTIHISTAMINE / NASAL DECONGESTANT

Each teaspoonful (5 mL) contains:

CODEINE PHOSPHATE...........................9 mg

*(WARNING: MAY BE HABIT-FORMING)

DEXCHLORPHENIRAMINE

MALEATE...............................................1 mg

PHENYLEPHRINE

HYDROCHLORIDE..................................5 mg

Cotton Candy Flavor

16 FL. OZ. (473 mL)

PRO-PHARMA LLC

"NEW FORMULATION"

Tamper evident by foil seal under cap. Do not use

if foil seal is broken or missing.

THIS BOTTLE NOT TO BE DISPENSED TO CONSUMER.

Dispense in a tight, light-resistant container with

a child-resistant cap.

Manufactured by:

Pernix Manufacturing, LLC

Houston, TX 77099

Distributed for:

Pro-Pharma, LLC

Kirksville, MO 63501

Rev. 09/13